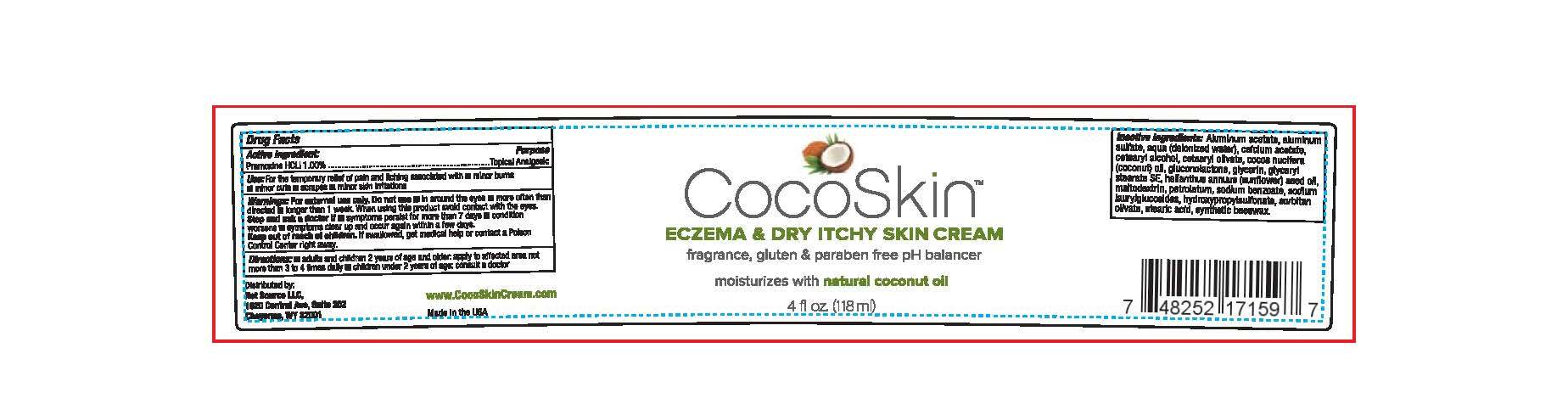 DRUG LABEL: COCOSKIN
NDC: 70678-001 | Form: CREAM
Manufacturer: Net Source, LLC
Category: otc | Type: HUMAN OTC DRUG LABEL
Date: 20160420

ACTIVE INGREDIENTS: PRAMOXINE HYDROCHLORIDE 1.18 mg/1 mL
INACTIVE INGREDIENTS: WATER; CALCIUM ACETATE; CETOSTEARYL ALCOHOL; HELIANTHUS ANNUUS WHOLE; PETROLATUM; SODIUM BENZOATE; SODIUM DECYLGLUCOSIDE HYDROXYPROPYLSULFONATE; SORBITAN OLIVATE; YELLOW WAX; ALUMINUM ACETATE; ALUMINUM SULFATE; GLUCONOLACTONE; GLYCERIN; GLYCERYL STEARATE SE; MALTODEXTRIN; CETEARYL OLIVATE; COCOS NUCIFERA WHOLE; SODIUM LAURYL GLYCOL CARBOXYLATE; STEARIC ACID

COCOSKIN

ACTIVE INGREDIENT

Pramoxine HCLI 1.00%

PURPOSE

Topical Analgesic

Keep out of reach of children. If swallowed get medical help or contact a poison control center right away.

DOSAGE AND ADMINISTRATION

Adults and children 2 years of age and older: apply to affected area not more than 3 to 4 times daily

Children under 2 years of age consult a doctor

WARNINGS

For external use only

Do not use: in around the eyes; more oftehn than directed; longer than 1 week

When using this product avoid contact with the eyes

Stop and ask a doctor if: sysmptoms persist for more than 7 days; conditions worsens; symptoms clear up and occur again within a few days

INACTIVE INGREDIENT

Aluminum acetate, aluminum sulfate, water, calcium acetate, cetearyl alcohol, cetearyl olivate, cocos nucifera oil, gluconolactone, glycerin, glyceryl sterate SE, sunflower seed oil, maltodextrin, petrolatum, sodium benzoate, sodium laurylglucosides, hydroxypropylsulfonate, sorbitan olivate, stearic acid, synthetic beeswax.

INDICATIONS AND USAGE

For the temporary relief of pain and itching associated with: minor burns, minor cuts, scrapes, minor skin irritations